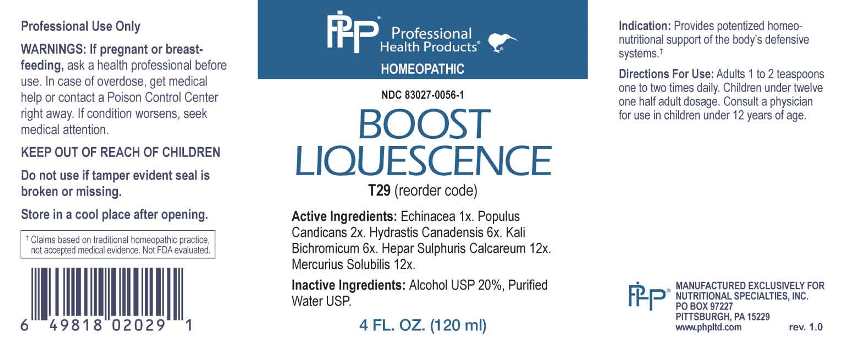 DRUG LABEL: Boost Liquescence
NDC: 83027-0056 | Form: LIQUID
Manufacturer: Nutritional Specialties, Inc.
Category: homeopathic | Type: HUMAN OTC DRUG LABEL
Date: 20230417

ACTIVE INGREDIENTS: ECHINACEA ANGUSTIFOLIA WHOLE 1 [hp_X]/1 mL; POPULUS BALSAMIFERA LEAF BUD 2 [hp_X]/1 mL; GOLDENSEAL 6 [hp_X]/1 mL; POTASSIUM DICHROMATE 6 [hp_X]/1 mL; CALCIUM SULFIDE 12 [hp_X]/1 mL; MERCURIUS SOLUBILIS 12 [hp_X]/1 mL
INACTIVE INGREDIENTS: WATER; ALCOHOL

DRUG FACTS:

ACTIVE INGREDIENTS:

Echinacea Angustifolia 1X, Populus Candicans 2X, Hydrastis Canadensis 6X, Kali Bichromicum 6X, Hepar Sulphuris Calcareum 12X, Mercurius Solubilis 12X.

PURPOSE:

Provides potentized homeo-nutritional support of the body's defensive systems.†

†Claims based on traditional homeopathic practice, not accepted medical evidence. Not FDA evaluated.

WARNINGS:

Professional Use Only

If pregnant or breast-feeding, ask a health professional before use.

In case of overdose, get medical help or contact a Poison Control Center right away.

If condition worsens, seek medical attention.

KEEP OUT OF REACH OF CHILDREN

Do not use if tamper evident seal is broken or missing.

Store in a cool place after opening

KEEP OUT OF REACH OF CHILDREN:

In case of overdose, get medical help or contact a Poison Control Center right away.

DIRECTIONS:

Adults 1 to 2 teaspoons one to two times daily. Children under twelve one half adult dosage. Consult a physician for use in children under 12 years of age.

INDICATIONS

Provides potentized homeo-nutritional support of the body's defensive systems.†

†Claims based on traditional homeopathic practice, not accepted medical evidence. Not FDA evaluated.

INACTIVE INGREDIENTS:

Alcohol USP 20%, Purified Water USP.

QUESTIONS:

MANUFACTURED EXCLUSIVELY FOR

NUTRITIONAL SPECIALTIES, INC.

PO BOX 97227

PITTSBURG, PA 15229

www.phpltd.com

PACKAGE LABEL DISPLAY:

Professional

Health Products

HOMEOPATHIC

NDC 83027-0056-1

BOOST

LIQUESCENCE

4 FL. OZ (120 ml)